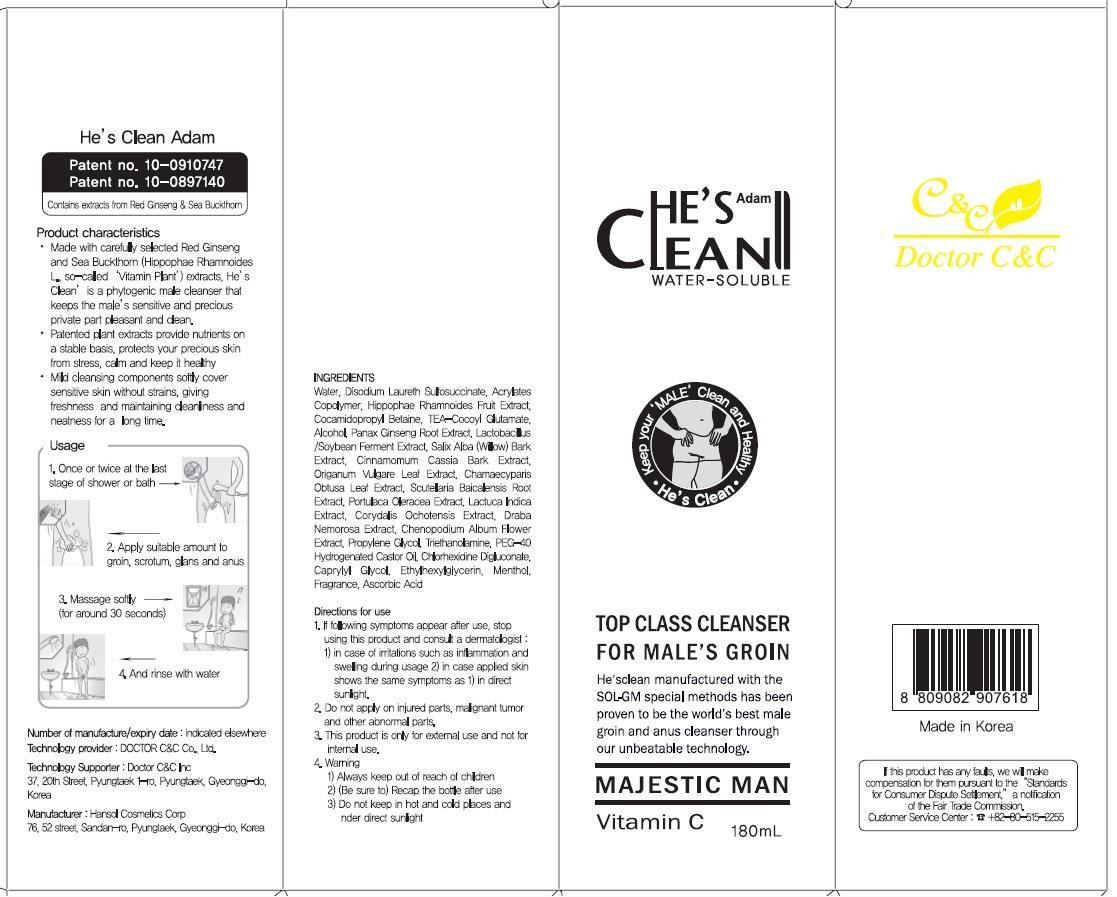 DRUG LABEL: HES CLEAN ADAM
NDC: 42979-120 | Form: GEL
Manufacturer: DOCTOR C&C
Category: otc | Type: HUMAN OTC DRUG LABEL
Date: 20140514

ACTIVE INGREDIENTS: Alcohol 5.4 mg/180 mL
INACTIVE INGREDIENTS: Water; Menthol

ACTIVE INGREDIENT

Active Ingredient: Alcohol 3%

INACTIVE INGREDIENT

Inactive ingredients:
Water, Disodium Laureth Sulfosuccinate, Acrylates Copolymer, Hippophae Rhamnoides Fruit Extract, Cocamidopropyl Betaine, TEA-Cocoyl Glutamate, Panax Ginseng Root Extract, Lactobacillus/Soybean Ferment Extract, Salix Alba (Willow) Bark Extract, Cinnamomum Cassia Bark Extract, Origanum Vulgare Leaf Extract, Chamaecyparis Obtusa Leaf Extract, Scutellaria Baicalensis Root Extract, Portulaca Oleracea Extract, Lactuca Indica Extract, Corydalis Ochotensis Extract, Draba Nemorosa Extract, Chenopodium Album Flower Extract, Propylene Glycol,
Triethanolamine, PEG-40 Hydrogenated Castor Oil, Chlorhexidine Digluconate, Caprylyl Glycol, Ethylhexylglycerin, Menthol, Fragrance, Ascorbic Acid

PURPOSE

Purpose: Sanitizer

WARNING

1. Always keep out of reach of children
2. Recap the bottle after use
3. Do not keep in hot and cold places and under direct sunlight

KEEP OUT OF REACH OF CHILDREN

Always keep out of reach of children

Product Characteristics

Mild cleansing components softly cover sensitive skin without strains, giving freshness and maintaining cleanliness and neatness for a long time.

Directions for use

1. If following sympoms appear after use, stop using this product and consult a dermatologist:
1) in case of irritations such as inflammation and swelling during usage
2) in case applied skin shows the same symptoms as 1) in direct sunlight.
2. Do not apply on injuries parts, malignant tumor and other abnormal parts.
3. This product is only for external use and not for internal use.